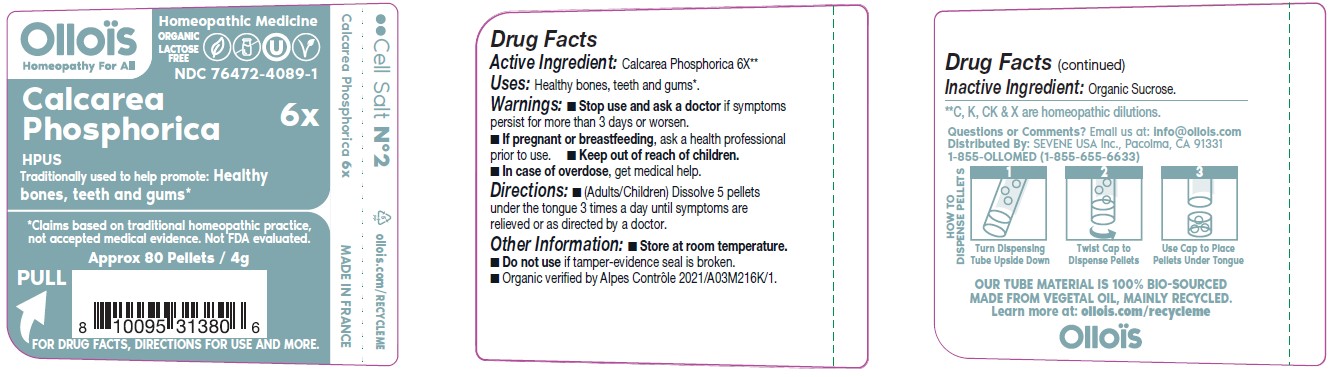 DRUG LABEL: CALCAREA PHOSPHORICA

NDC: 76472-4089 | Form: PELLET
Manufacturer: SEVENE USA
Category: homeopathic | Type: HUMAN OTC DRUG LABEL
Date: 20250211

ACTIVE INGREDIENTS: TRIBASIC CALCIUM PHOSPHATE 6 [hp_X]/1 1
INACTIVE INGREDIENTS: SUCROSE

SEVENE USA (as PLD) - CALCAREA PHOSPHORICA 6X (76472-4089)

ACTIVE INGREDIENT:

CALCAREA PHOSPHORICA 6X**

**C, K, CK & X are homeopathic dilutions.

TRADITIONALLY USED TO HELP PROMOTE:

Healthy bones, teeth and gums*

*Claims based on traditional homeopathic practice, not accepted medical evidence. Not FDA evaluated.

DIRECTIONS:

- (Adults/Children) Dissolve 5 pellets under the tongue three times a day until symptoms are relieved or as directed by a doctor.

USES:

Healthy bones, teeth and gums*.

WARNINGS

- Stop use and ask a doctor if symptoms persist for more than 3 days or worsen.

PREGNANCY OR BREAST FEEDING

- If pregnant or breast-feeding, ask a health professional before use.

- Keep out of reach of children.
- In case of overdose, get medical help.

OTHER INFORMATION:

- Store at room temperature.
- Do not use if tamper-evidence seal is broken.
- Organic verified by Alpes Control 2021/A03M216K/1.

INACTIVE INGREDIENT:

ORGANIC SUCROSE

QUESTIONS OR COMMENTS?

Email us at: info@ollois.com